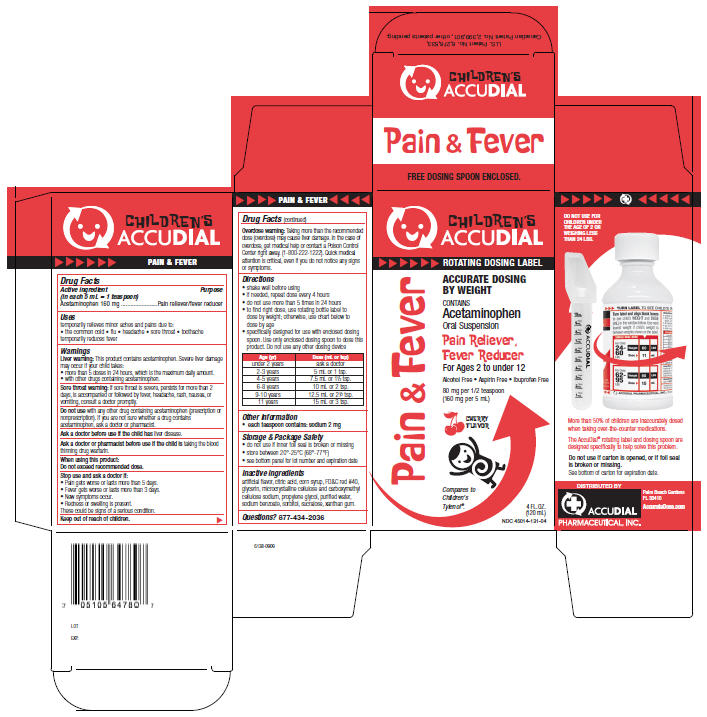 DRUG LABEL: Pain and Fever
NDC: 45014-131 | Form: SUSPENSION
Manufacturer: Accudial Pharmaceutical, Inc.
Category: otc | Type: HUMAN OTC DRUG LABEL
Date: 20100119

ACTIVE INGREDIENTS: Acetaminophen 160 mg/5 mL
INACTIVE INGREDIENTS: Cherry; Citric Acid Monohydrate; Corn Syrup; FD&C RED NO. 40; Glycerin; Cellulose, Microcrystalline; CarboxymethylCellulose Sodium; Propylene Glycol; Water; Sodium benzoate; Sucralose; Sorbitol; Xanthan Gum

CHILDREN'S
ACCUDIAL
Pain & Fever

Drug Facts

Active ingredient (in each 5 mL = 1 teaspoon)

Acetaminophen 160 mg

Purpose

Pain reliever/fever reducer

Uses

temporarily relieves minor aches and pains due to:

- the common cold
- flu
- headache
- sore throat
- toothache

temporarily reduces fever

Warnings

Liver warning

This product contains acetaminophen. Severe liver damage may occur if your child takes:

- more than 5 doses in 24 hours, which is the maximum daily amount.
- with other drugs containing acetaminophen.

Sore throat warning

If sore throat is severe, persists for more than 2 days, is accompanied or followed by fever, headache, rash, nausea, or vomiting, consult a doctor promptly.

Do not use with any other drug containing acetaminophen (prescription or nonprescription). If you are not sure whether a drug contains acetaminophen, ask a doctor or pharmacist.

Ask a doctor before use if the child has liver disease.

Ask a doctor or pharmacist before use if the child is taking the blood thinning drug warfarin.

When using this product

Do not exceed recommended dose.

Stop use and ask a doctor if

- Pain gets worse or lasts more than 5 days.
- Fever gets worse or lasts more than 3 days.
- New symptoms occur.
- Redness or swelling is present.

These could be signs of a serious condition.

Keep out of reach of children.

Overdose warning

Taking more than the recommended dose (overdose) may cause liver damage. In the case of overdose, get medical help or contact a Poison Control Center right away. (1-800-222-1222). Quick medical attention is critical, even if you do not notice any signs or symptoms.

Directions

- shake well before using
- if needed, repeat dose every 4 hours
- do not use more than 5 times in 24 hours
- to find right dose, use rotating bottle label to dose by weight; otherwise, use chart below to dose by age
- specifically designed for use with enclosed dosing spoon. Use only enclosed dosing spoon to dose this product. Do not use any other dosing device

Age (yr) | Dose (mL or tsp)
under 2 years | ask a doctor
2-3 years | 5 mL or 1 tsp.
4-5 years | 7.5 mL or 1½ tsp.
6-8 years | 10 mL or 2 tsp.
9-10 years | 12.5 mL or 2½ tsp.
11 years | 15 mL or 3 tsp.

Other information

- each teaspoon contains: sodium 2 mg

Storage & Package Safety

- do not use if inner foil seal is broken or missing
- store between 20°-25°C (68°-77°F)
- see bottom panel for lot number and expiration date

Inactive ingredients

artificial flavor, citric acid, corn syrup, FD&C red #40, glycerin, microcrystalline cellulose and carboxymethyl cellulose sodium, propylene glycol, purified water, sodium benzoate, sorbitol, sucralose, xanthan gum.

Questions?

877-434-2036

PRINCIPAL DISPLAY PANEL - 120 mL Carton

CHILDREN'S
ACCUDIAL

ROTATING DOSING LABEL

ACCURATE DOSING BY WEIGHT

CONTAINS
Acetaminophen
Oral Suspension

Pain Reliever,
Fever Reducer
For Ages 2 to under 12

Alcohol Free • Aspirin Free • Ibuprofen Free

80 mg per 1/2 teaspoon
(160 mg per 5 mL)

CHERRY
FLAVOR

Compares to
Children's
Tylenol ®.

4 FL.OZ.
(120 mL)
NDC 45014-131-04